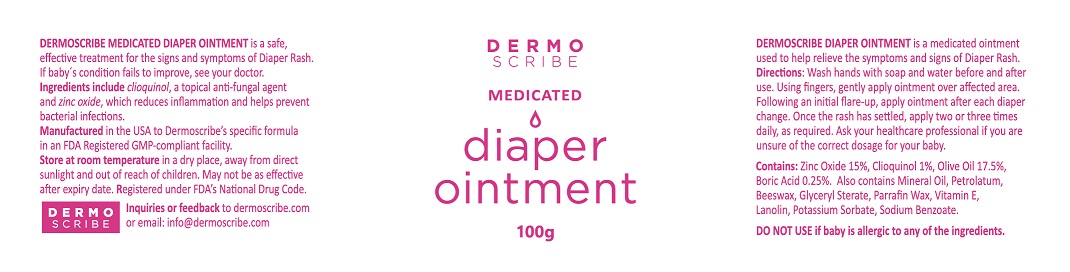 DRUG LABEL: DERMOSCRIBE DIAPER
NDC: 69683-102 | Form: OINTMENT
Manufacturer: DERMOSCRIBE PTY LTD
Category: otc | Type: HUMAN OTC DRUG LABEL
Date: 20221222

ACTIVE INGREDIENTS: CLIOQUINOL 1 g/100 g; ZINC OXIDE 15 g/100 g
INACTIVE INGREDIENTS: OLIVE OIL; BORIC ACID; MINERAL OIL; PETROLATUM; YELLOW WAX; GLYCERYL MONOSTEARATE; PARAFFIN; .ALPHA.-TOCOPHEROL ACETATE; LANOLIN; POTASSIUM SORBATE; SODIUM BENZOATE

DERMOSCRIBE - DIAPER OINTMENT (69683-102)

ACTIVE INGREDIENTS:

ZINC OXIDE 15%

CLIOQUINOL 1%

PURPOSE

ANTIFUNGAL

ANTIBACTERIAL

USES

A SAFE, EFFECTIVE TREATMENT FOR THE SIGNS AND SYMPTOMS OF DIAPER RASH.

REDUCES INFLAMMATION AND HELPS PREVENT BACTERIAL INFECTIONS.

WARNINGS

FOR EXTERNAL USE ONLY

IF BABY'S CONDITION FAILS TO IMPROVE, SEE YOUR DOCTOR.

DO NOT USE IF BABY IS ALLERGIC TO ANY OF THE INGREDIENTS.

KEEP OUT OF REACH OF CHILDREN.

DIRECTIONS:

WASH HANDS WITH SOAP AND WATER BEFORE AND AFTER USE. USING FINGERS, GENTLY APPLY OINTMENT OVER AFFECTED AREA. FOLLOWING AN INITIAL FLARE-UP, APPLY OINTMENT AFTER EVERY DIAPER CHANGE. ONCE THE RASH HAS SETTLED, APPLY TWO OR THREE TIMES DAILY, AS REQUIRED. ASK YOUR HEALTHCARE PROFESSIONAL IF YOU ARE UNSURE OF THE CORRECT DOSAGE FOR YOUR BABY.

INACTIVE INGREDIENTS

OLIVE OIL 17.5%, BORIC ACID 0.25%, MINERAL OIL, PETROLATUM, BEESWAX, GLYCERYL STEARATE, PARAFFIN WAX, VITAMIN E, LANOLIN, POTASSIUM SORBATE, SODIUM BENZOATE.

OTHER SAFETY INFORMATION

STORE AT ROOM TEMPERATURE IN A DRY PLACE, AWAY FROM DIRECT SUNLIGHT AND OUT OF REACH OF CHILDREN. MAY NOT BE AS EFFECTIVE AFTER EXPIRY DATE.